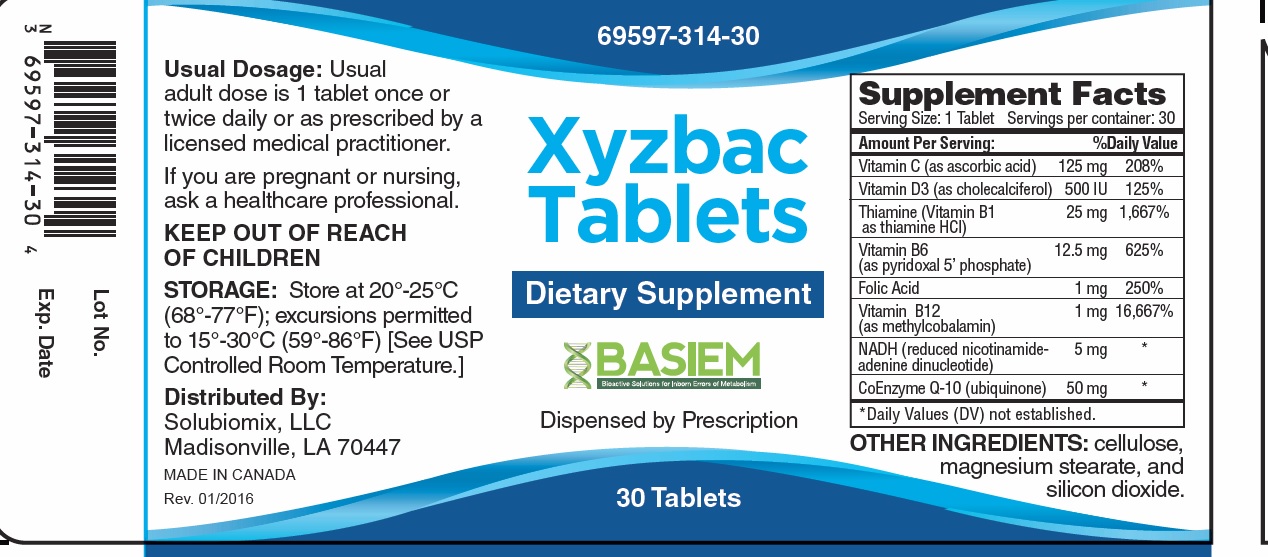 DRUG LABEL: Xyzbac
NDC: 69597-314 | Form: TABLET
Manufacturer: Basiem
Category: other | Type: DIETARY SUPPLEMENT
Date: 20251006

ACTIVE INGREDIENTS: ASCORBIC ACID 125 mg/1 1; cholecalciferol 500 [iU]/1 1; THIAMINE HYDROCHLORIDE 25 mg/1 1; PYRIDOXAL PHOSPHATE ANHYDROUS 12.5 mg/1 1; FOLIC ACID 1 mg/1 1; METHYLCOBALAMIN 1 mg/1 1; NADH 5 mg/1 1; COENZYME Q10, (2Z)- 50 mg/1 1
INACTIVE INGREDIENTS: CELLULOSE, MICROCRYSTALLINE; MAGNESIUM STEARATE; SILICON DIOXIDE

Xyzbac

HEALTH CLAIM

Xyzbac Tablets Dietary Supplement

Dispensed by Prescription†

Supplement Facts
Serving Size: 1 Tablet
Servings per Bottle: 30
Amount Per Serving: | % Daily Value
Vitamin C (as ascorbic acid) | 125 mg | 208%
Vitamin D3 (as cholecalciferol) | 500 IU | 125%
Thiamin (Vitamin B1 as thiamin HCl) | 25 mg | 1,667%
Vitamin B6 (as pyridoxal 5’ phosphate) | 12.5 mg | 625%
Folic Acid | 1 mg | 250%
Vitamin B12 (as methylcobalamin) | 1 mg | 16,667%
NADH (reduced nicotinamide-adenine dinucleotide) | 5 mg | *
CoEnzyme Q-10 (ubiquinone) | 50 mg | *
*Daily Values (DV) not established.

OTHER INGREDIENTS: cellulose, magnesium stearate, and silicon dioxide.

DESCRIPTION:

Xyzbac Tablets is an orally administered prescription vitamin formulation for the clinical dietary management of suboptimal nutritional status in patients where advanced folate supplementation is required and nutritional supplementation in physiologically stressful conditions for maintenance of good health is needed.

WARNING AND PRECAUTIONS

This product is contraindicated in patients with a known hypersensitivity to any of the ingredients.

Xyzbac tablets should only be used under the direction and supervision of a licensed medical practitioner. Use with caution in patients that may have a medical condition, are pregnant, lactating, trying to conceive, under the age of 18, or taking medications.

Pregnancy and Lactation
Xyzbac is not intended for use in pregnant or lactating patients.

DOSAGE & ADMINISTRATION

Usual adult dose is 1 tablet once or twice daily or as prescribed by a licensed medical practitioner.

HOW SUPPLIED HEALTH CLAIM:

Xyzbac tablets are supplied as tan, oblong shaped tablets with imprint “314”in a child-resistant bottle of 30ct. (69597-314-30*)

Dispensed by Prescription†

*Basiem does not represent these product codes to be National Drug Codes (NDC). Product codes are formatted according to standard industry practice, to meet the formatting requirement by pedigree reporting and supply-chain control including pharmacies.

† This product is a prescription-folate with or without other dietary ingredients that, due to increased folate levels increased risk associated with masking of B12 deficiency (pernicious anemia) requires administration under the care of a licensed medical practitioner (61 FR 8760).^1-3 The most appropriate way to ensure pedigree reporting consistent with these regulatory guidelines and safety monitoring is to dispense this product only by prescription (Rx). This is not an Orange Book product. This product may be administered only under a physician’s supervision and all prescriptions using this product shall be pursuant to state statutes as applicable. The ingredients, indication or claims of this product are not to be construed to be drug claims.

1. Federal Register Notice of August 2, 1973 (38 FR 20750)
2. Federal Register Notice of October 17, 1980 (45 FR 69043, 69044)
3. Federal Register Notice of March 5, 1996 (61 FR 8760)

STORAGE AND HANDLING:

Store at 20°-25°C (68°-77°F); excursions permitted to 15°-30°C (59°-86°F) [See USP Controlled Room Temperature.]

Protect from heat, light and moisture.

KEEP OUT OF THE REACH OF CHILDREN.

Tamper Evident: Do not use if seal is broken or missing.

To report adverse side effects or to obtain product information, contact Basiem, LLC at 1-844-551-9911